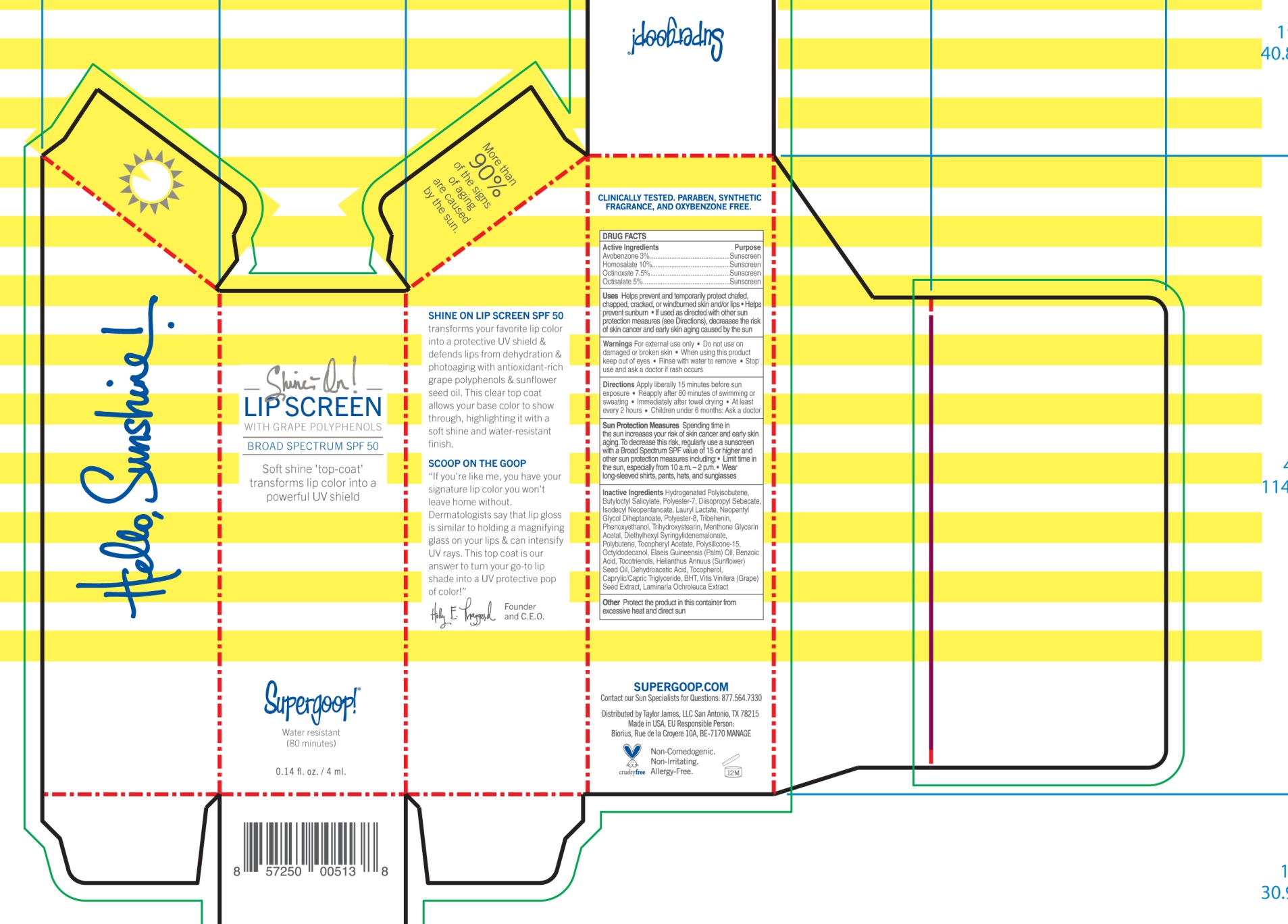 DRUG LABEL: Shine On Lip Sunscreen

NDC: 75936-141 | Form: CREAM
Manufacturer: TAYLOR JAMES, LTD.
Category: otc | Type: HUMAN OTC DRUG LABEL
Date: 20201112

ACTIVE INGREDIENTS: AVOBENZONE 3 g/100 mL; HOMOSALATE 10 g/100 mL; OCTINOXATE 7.5 g/100 mL; OCTISALATE 5 g/100 mL
INACTIVE INGREDIENTS: HYDROGENATED POLYBUTENE (1300 MW); BUTYLOCTYL SALICYLATE; POLYESTER-7; DIISOPROPYL SEBACATE; ISODECYL NEOPENTANOATE; LAURYL LACTATE; NEOPENTYL GLYCOL DIHEPTANOATE; POLYESTER-8 (1400 MW, CYANODIPHENYLPROPENOYL CAPPED); TRIBEHENIN; PHENOXYETHANOL; TRIHYDROXYSTEARIN; MENTHONE 1,2-GLYCEROL KETAL, (+/-)-; DIETHYLHEXYL SYRINGYLIDENEMALONATE; POLYBUTENE (1400 MW); .ALPHA.-TOCOPHEROL ACETATE; POLYSILICONE-15; OCTYLDODECANOL; PALM OIL; BENZOIC ACID; TOCOTRIENOLS; SUNFLOWER OIL; DEHYDROACETIC ACID; TOCOPHEROL; MEDIUM-CHAIN TRIGLYCERIDES; BUTYLATED HYDROXYTOLUENE; VITIS VINIFERA SEED; LAMINARIA OCHROLEUCA

Shine-On Lip Sunscreen Broad Spectrum SPF 50

Active Ingredients Purpose

Avobenzone 3% ............. Sunscreen

Homosalate 10% ............ Sunscreen

Octinoxate 7.5% ............ Sunscreen

Octisalate 5% ................ Sunscreen

Uses

- Helps prevent and tempararily protect chafed, chapped, cracked, or windburned skin and/or lips
- Helps prevent sunburn
- If used as directed with other sun protection measures (see Directions), decreases the risk of skin cancer and early skin aging caused by the sun

Children under 6 months: Ask a doctor

Stop use and ask a doctor if rash occurs

Warnings

- For external use only
- Do not use on damaged or broken skin
- When using this product keep out of eyes
- Rinse with water to remove

Directions

- Apply liberally 15 minuts before sun exposure
- Reapply after 80 minuts of swimming or sweating
- Immediately after towel drying
- At least every two hours

Sun Protection Measures: Spending time in the sun increases your risk of skin cancer and early skin aging. To decrease this risk, regularly use a sunscreen with a Broad Spectrum SPF value of 15 or higher and other sun protection measures including:

- Limit time in the sun, especially from 10a.m. - 2p.m.
- Wear long-sleeved shirts, pants, hats, and sunglasses

Inactive Ingredients

Hydrogenated Polyisobutene, Butyloctyl Salicylate, Polyester-7, Diisopropyl Sebacte, Isodecyl Neopentanoate, Lauryl Lactate, Neopentyl Glycol Diheptanoate, Polyester-8, Tibehenin, Phenoxyethanol, Trihydroxystearin, Menthone Glycerin Acetal, Diethylhexy Syringylidenemalonate, Polybutene, Tocopheryl Acetate, Polysilicone-15, Octyldodecanol, Elaeis Guineensis (Palm) Oil, Benzoic Acid, Tocotrienols, Helianthus Annuus (Sunflower) Seed Oil, Dehydroacetic Acid, Tocopherol, Caprylic/Capric Triglyceride, BHT, Vits Vinifera (Grape) Seed Extract, Laminaria Ochroleuca Extract

PACKAGE LABEL

Shine-On!

Lip Screen

With Grape Polyphenols

Broa Spectrum SPF 50

Supergoop!

Water resistant

(80 minutes)

0.14 fl. oz. / 4 ml.